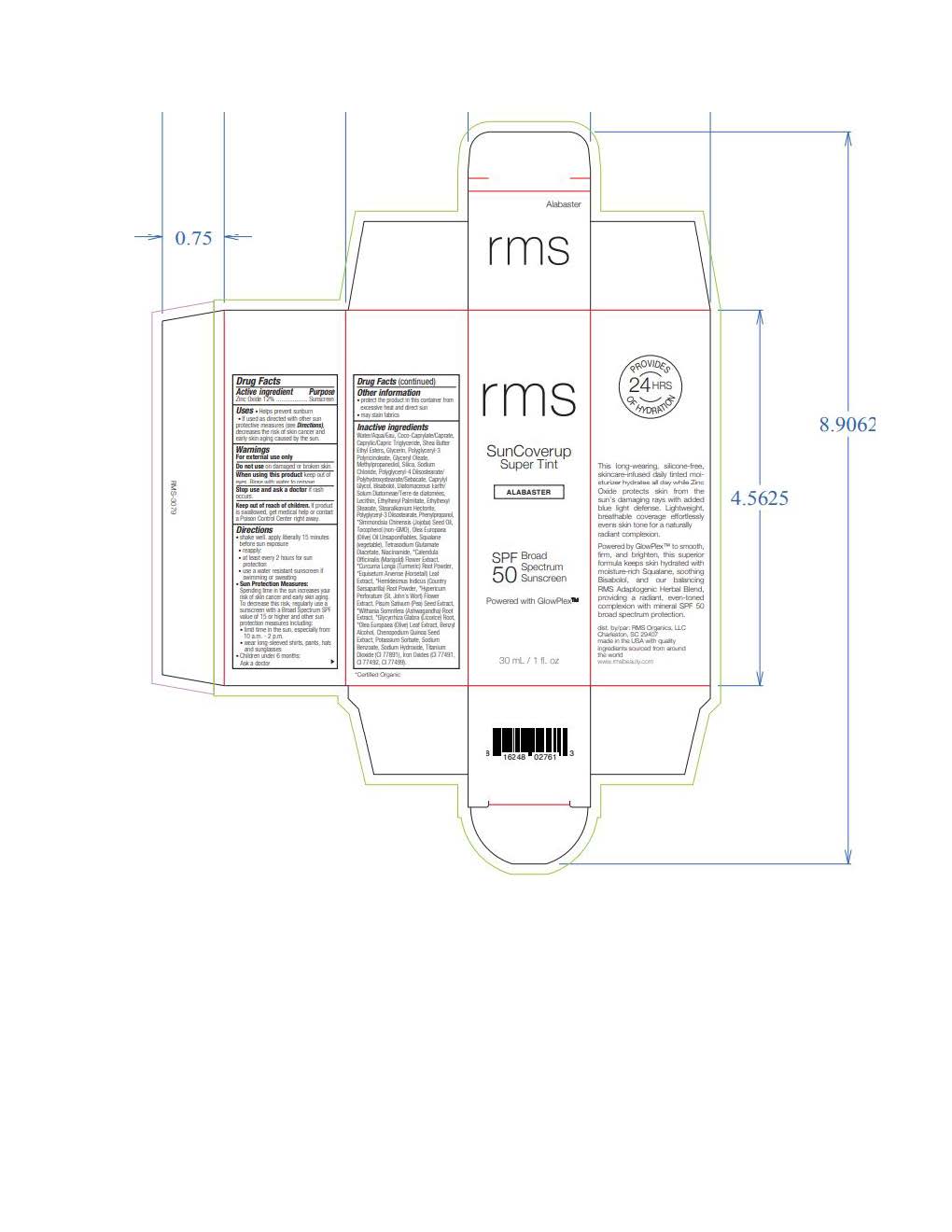 DRUG LABEL: rms SunCoverup Super Tint
NDC: 83249-213 | Form: LOTION
Manufacturer: RMS
Category: otc | Type: HUMAN OTC DRUG LABEL
Date: 20250814

ACTIVE INGREDIENTS: ZINC OXIDE 132 mg/1 mL
INACTIVE INGREDIENTS: EQUISETUM ARVENSE LEAF POWDER; OCTYL STEARATE; GLYCYRRHIZA GLABRA (LICORICE) ROOT; CHENOPODIUM QUINOA SEED; FERRIC OXIDE RED; DIATOMACEOUS EARTH; SQUALANE; CURCUMA LONGA (TURMERIC) ROOT; OLEA EUROPAEA (OLIVE) LEAF; WITHANIA SOMNIFERA ROOT; CAPRYLIC/CAPRIC TRIGLYCERIDE; BENZYL ALCOHOL; SODIUM BENZOATE; POTASSIUM SORBATE; HYPERICUM PERFORATUM FLOWER; GLYCERYL OLEATE; OLEA EUROPAEA (OLIVE) OIL UNSAPONIFIABLES; SODIUM HYDROXIDE; TETRASODIUM GLUTAMATE DIACETATE; SODIUM CHLORIDE; POLYGLYCERYL-4 DIISOSTEARATE/POLYHYDROXYSTEARATE/SEBACATE; WATER; NIACINAMIDE; COCO-CAPRYLATE/CAPRATE; .ALPHA.-BISABOLOL, (+)-; PISUM SATIVUM WHOLE; LECITHIN, SOYBEAN; FERRIC OXIDE YELLOW; SIMMONDSIA CHINENSIS (JOJOBA) SEED OIL; TITANIUM DIOXIDE; SILICON DIOXIDE; TOCOPHEROL; CAPRYLYL GLYCOL; PHENYLPROPANOL; METHYLPROPANEDIOL; POLYGLYCERYL-3 DIISOSTEARATE; GLYCERIN; STEARALKONIUM HECTORITE; SHEA BUTTER ETHYL ESTERS; CALENDULA OFFICINALIS FLOWER; HEMIDESMUS INDICUS ROOT; FERROSOFERRIC OXIDE; ETHYLHEXYL PALMITATE

rms SunCoverup Super Tint